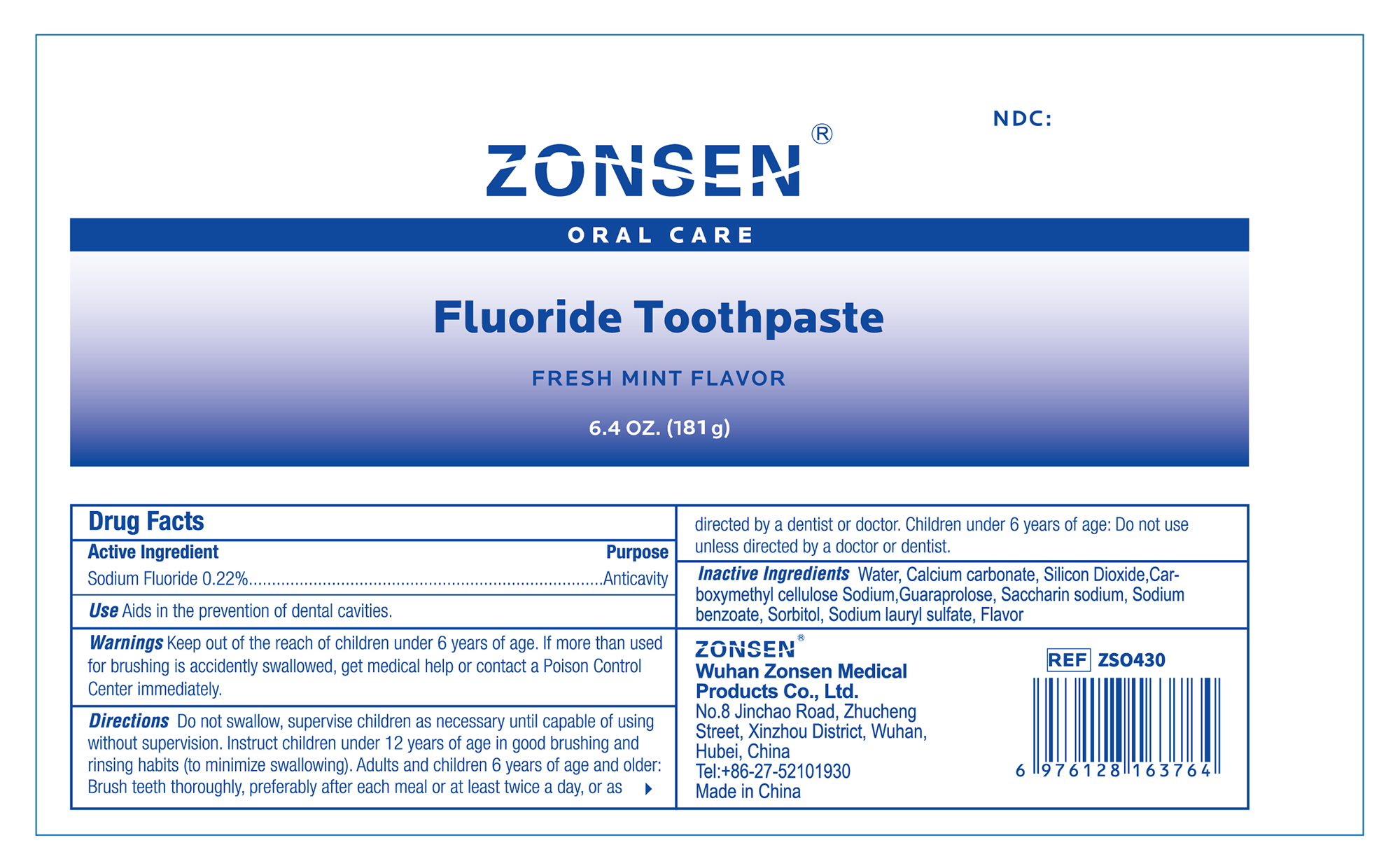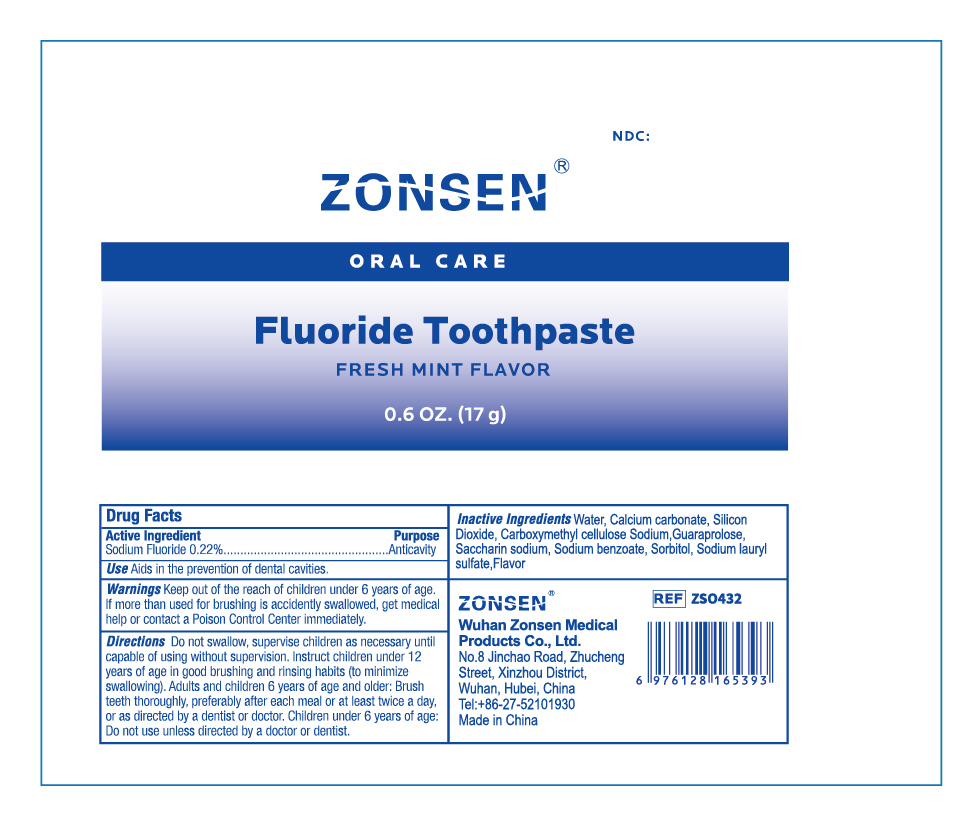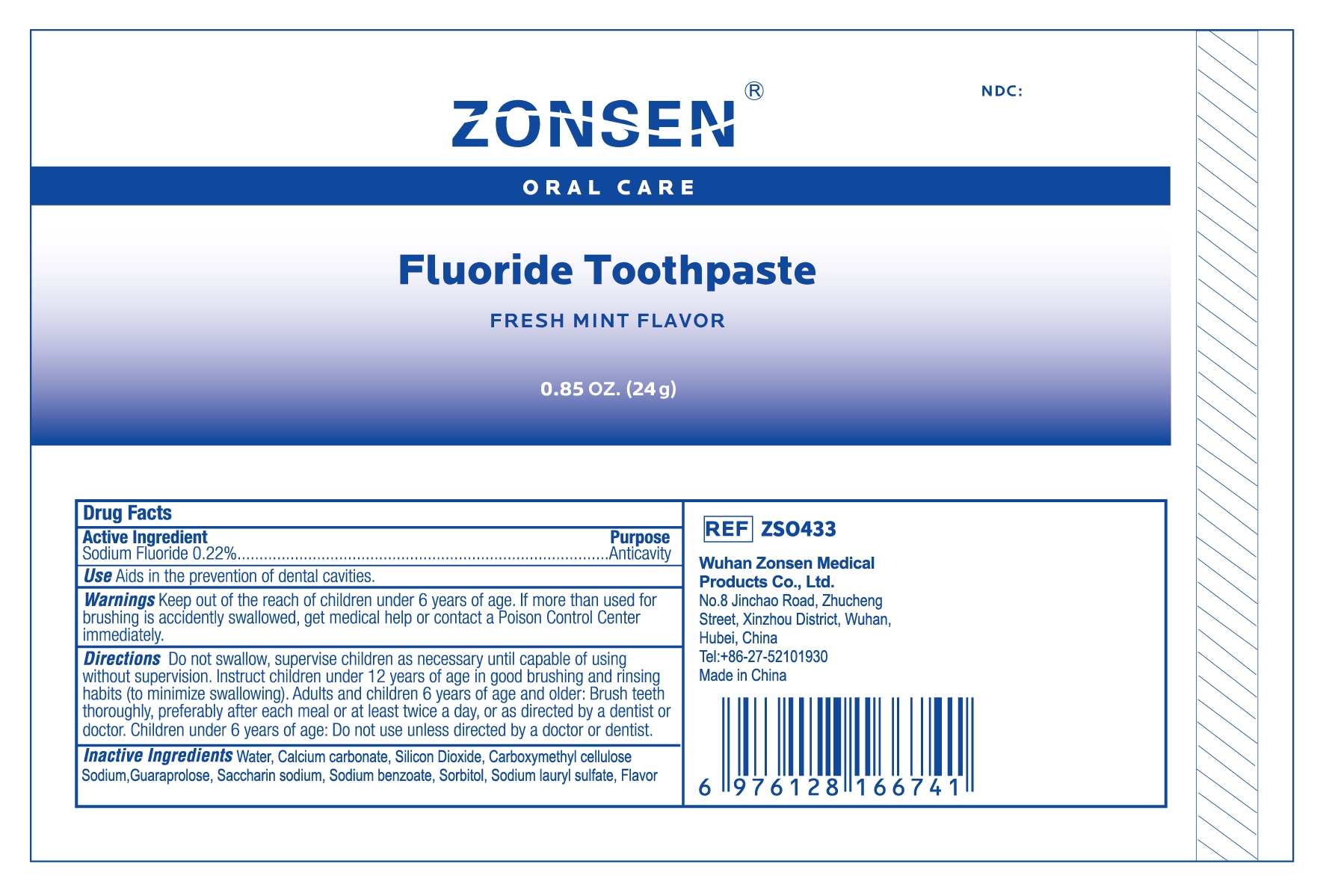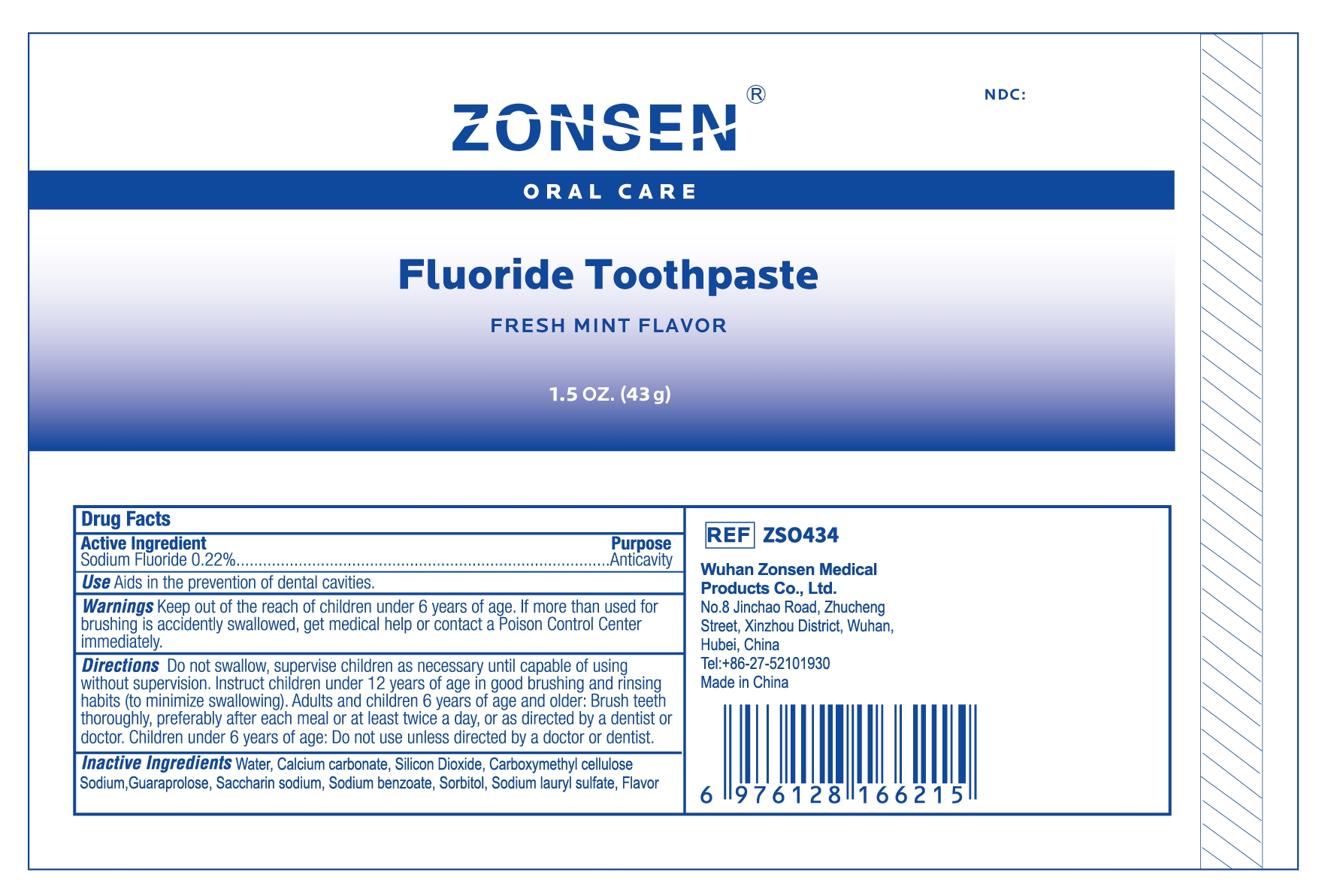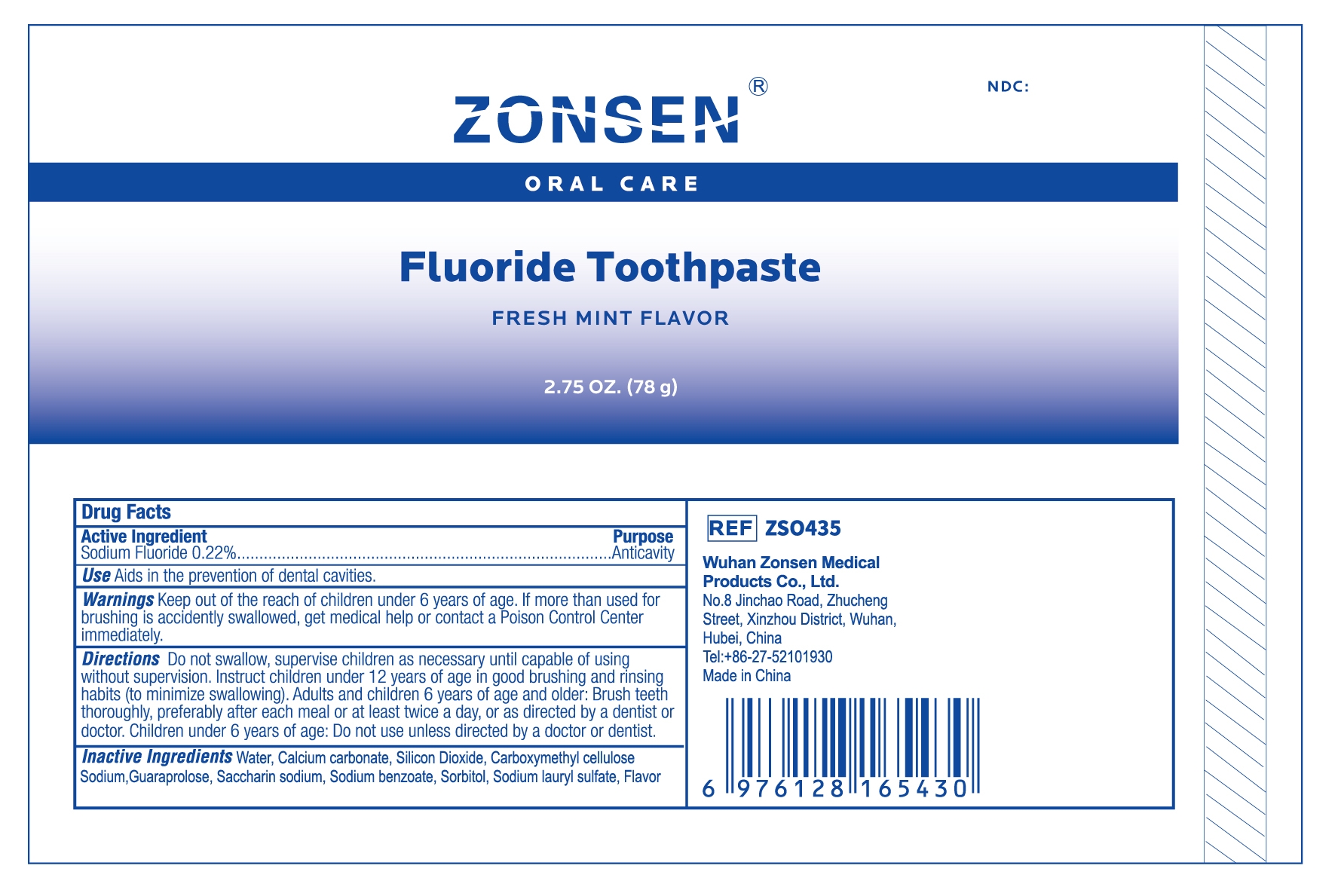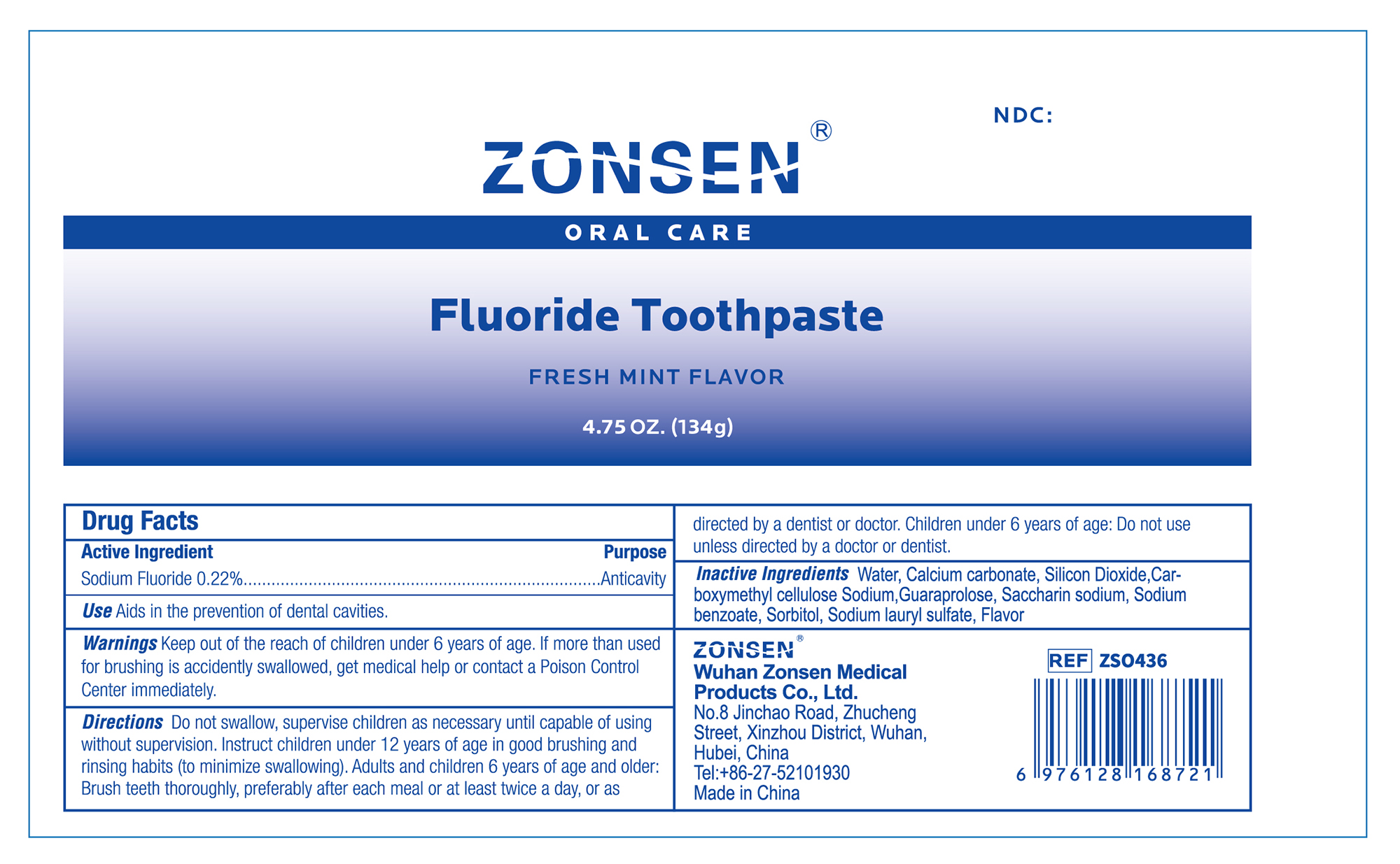 DRUG LABEL: ZONSEN Toothpaste,white
NDC: 72932-016 | Form: PASTE, DENTIFRICE
Manufacturer: Wuhan Zonsen Medical Products Co., Ltd.
Category: otc | Type: HUMAN OTC DRUG LABEL
Date: 20250211

ACTIVE INGREDIENTS: SODIUM FLUORIDE 0.22 g/100 g
INACTIVE INGREDIENTS: SODIUM LAURYL SULFATE; SILICON DIOXIDE; SODIUM BENZOATE; SORBITOL; CARBOXYMETHYLCELLULOSE SODIUM; GUARAPROLOSE (1300 MPA.S AT 1%); SACCHARIN SODIUM; CALCIUM CARBONATE; WATER

ZONSEN Fluoride Toothpaste

ACTIVE INGREDIENT

Sodium Fluoride 0.22%

PURPOSE

Anticavity

INDICATIONS AND USAGE

Aids in the prevention of dental cavities.

WARNINGS

Keep out of the reach of children under 6 years of age. If more than used for brushing is accidently swallowed, get medical help or contact a Poison Control Center immediately.

DOSAGE AND ADMINISTRATION

Do not swallow, supervise children as necessary until capable of using without supervision. Instruct Children under 12 years of age in good brushing and rinsing habits (to minimize swallowing). Adults and children 6 years of age and older: Brush teeth thoroughly, preferably after each meal or at least twice a day, or as directed by a dentist or doctor. Children under 6 years of age: Do not use unless directed by a doctor or dentist.

INACTIVE INGREDIENT

Water, Calcium carbonate, Silicon Dioxide, Carboxymethyl cellulose Sodium,Guaraprolose, Saccharin sodium, Sodium benzoate, Sorbitol, Sodium lauryl sulfate, flavor

KEEP OUT OF REACH OF CHILDREN

Keep out of the reach of children under 6 years of age. If more than used for brushing is accidently swallowed, get medical help or contact a Poison Control Center immediately.

PACKAGE LABEL

ZONSEN NDC:72932-016-00

Oral Care

Fluoride Toothpaste

FRESH MINT FLAVOR

0.6 OZ. (17 g)

PACKAGE LABEL

ZONSEN NDC:72932-016-01

Oral Care

Fluoride Toothpaste

FRESH MINT FLAVOR

0.85 OZ. (24 g)

PACKAGE LABEL

ZONSEN NDC: 72932-016-02

Oral Care

Fluoride Toothpaste

FRESH MINT FLAVOR

1.5 OZ. (43 g)

PACKAGE LABEL

ZONSEN NDC:72932-016-03

Oral Care

Fluoride Toothpaste

FRESH MINT FLAVOR

2.75 OZ. (78 g)

PACKAGE LABEL

ZONSEN NDC:72932-016-04

Oral Care

Fluoride Toothpaste

FRESH MINT FLAVOR

4.75 OZ. (134 g)

PACKAGE LABEL

ZONSEN NDC:72932-016-05

Oral Care

Fluoride Toothpaste

FRESH MINT FLAVOR

6.4 OZ. (181 g)